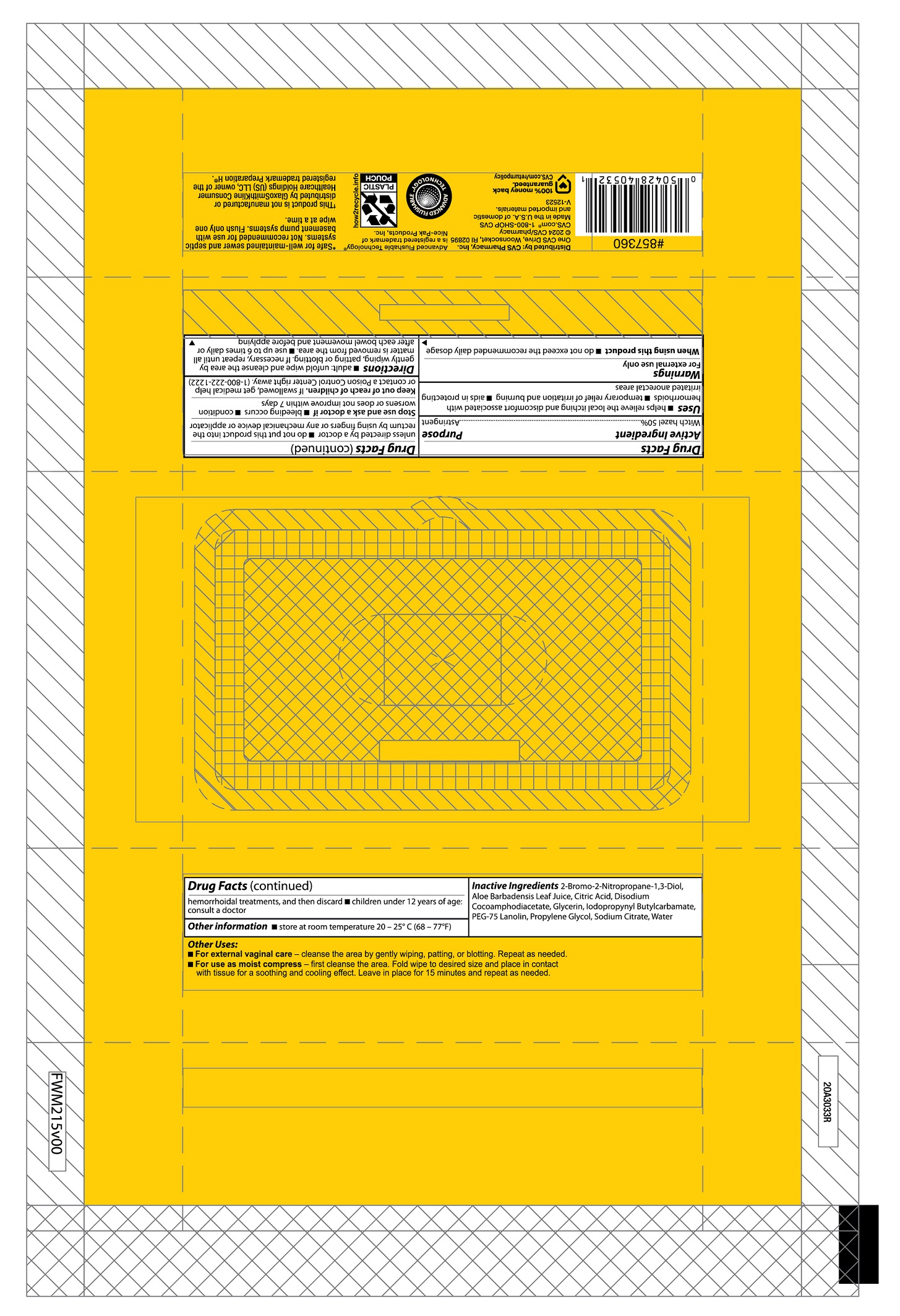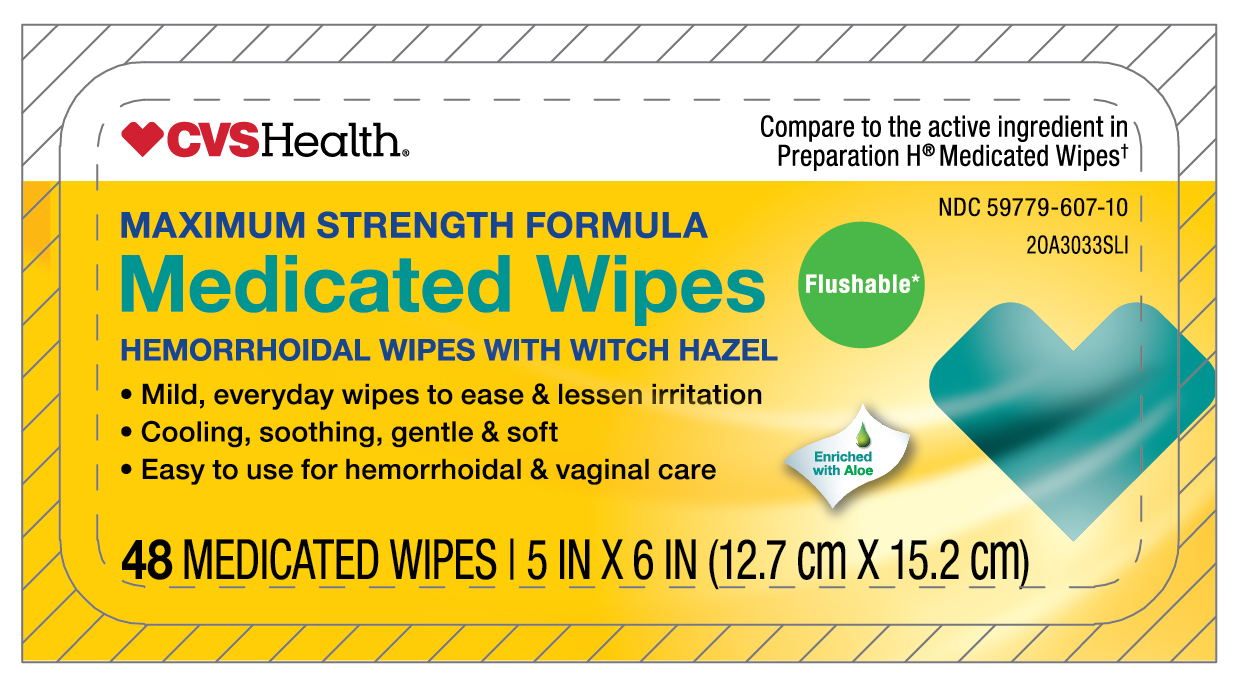 DRUG LABEL: Medicated Wipes

NDC: 59779-607 | Form: CLOTH
Manufacturer: CVS Pharmacy
Category: otc | Type: HUMAN OTC DRUG LABEL
Date: 20251205

ACTIVE INGREDIENTS: WITCH HAZEL 0.5 g/1 g
INACTIVE INGREDIENTS: WATER; GLYCERIN; PROPYLENE GLYCOL; SODIUM CITRATE; CITRIC ACID MONOHYDRATE; IODOPROPYNYL BUTYLCARBAMATE; DISODIUM COCOAMPHODIACETATE; BRONOPOL; ALOE VERA LEAF; PEG-75 LANOLIN

MEDICATED WIPES HEMORRHOIDAL WIPES WITH WITCH HAZEL

Active ingredient

Witch hazel 50%

Purpose

Astringent

Uses

- helps relieve the local itching and discomfort associated with hemorrhoids
- temporary relief of irritation and burning
- aids in protecting irritated anorectal areas

Warnings

For external use only

When using this product

- do not exceed the recommended daily dosage unless directed by a doctor
- do not put this product into the rectum by using fingers or any mechanical device or applicator

Stop use and ask a doctor if

- bleeding occurs
- condition worsens or does not improve within 7 days

Keep Out of Reach of Children.

If swallowed, get medical help or contact a Poison Control Center right away.

Directions

- adults: unfold wipe and cleanse the area by gently wiping, patting or blotting. If necessary, repeat until all matter is removed from the area
- use up to 6 times daily or after each bowel movement and before applying hemorrhoidal treatments, and then discard
- children under 12 years of age: consult a doctor

Other information

- store at room temperature 20 - 25oC (68 - 77oF)

Inactive ingredients

2-Bromo-2-Nitropropane-1,3-Diol, Aloe Barbadensis Leaf Juice, Citric Acid, Disodium Cocoamphodiacetate, Glycerin, Iodopropynyl Butylcarbamate, PEG-75 Lanolin, Propylene Glycol, Sodium Citrate, Water

Distributed by:

CVS Pharmacy, Inc.
One CVS Drive
Woonsocket, RI 02895

CVS/pharmacy
www.cvs.com
1-800-shop-CVS

*This product is not manufactured or distributed by GlaxoSmithKline Consumer Healthcare Holdings (US) LLC, owner of the registered trademark of Preparation H(R)